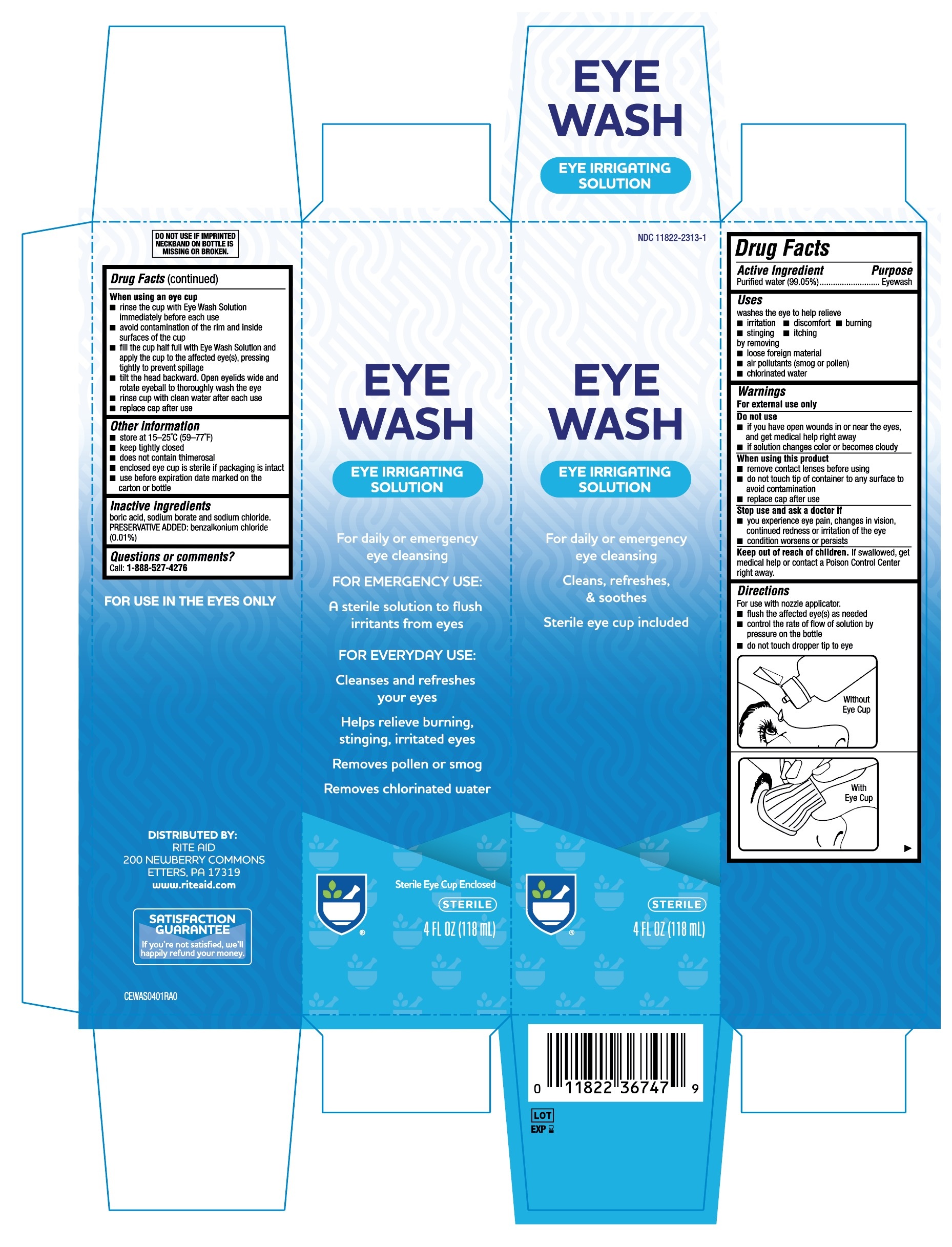 DRUG LABEL: Rite Aid Eye Wash
NDC: 11822-2313 | Form: SOLUTION
Manufacturer: Rite Aid
Category: otc | Type: HUMAN OTC DRUG LABEL
Date: 20251230

ACTIVE INGREDIENTS: WATER 99.05 g/100 mL
INACTIVE INGREDIENTS: SODIUM BORATE; BORIC ACID; BENZALKONIUM CHLORIDE; SODIUM CHLORIDE

Rite Aid Eye Wash 118mL (PLD)

Active ingredient

Purified water (99.05%)

Purpose

Eyewash

Uses

washes the eye to help relieve

- irritation
- stinging
- discomfort
- itching
- burning

by removing

- loose foreign material
- air pollutants(smog or pollen)
- chlorinated water

Warnings

For external use only

Do not use

- if you have open wounds in or near the eyes, and get medical help right away
- if solution changes color or becomes cloudy

When using this product

- remove contact lenses before using
- do not touch tip of container to any surface to avoid contamination
- replace cap after use

Stop use and ask a doctor if

- you experience eye pain, changes in vision, continued redness or irritation of the eye
- condition worsens or persists

Keep out of reach of children.

If swallowed, get medical help or contact a Poison Control Center right away.

Directions

For use with nozzle applicator.

- flush the affected eye(s) as needed
- control the rate of flow of solution by pressure on the bottle
- do not touch dropper tip to eye

When using an eye cup

- rinse the cup with Eye Wash Solution Immediately before each use
- avoid contamination of the rim and inside surfaces of the cup
- fill the cup half full with Eye Wash Solution and apply the cup to affected eye(s), pressing tightly to avoid spillage
- tilt the head backward. Open eyelids wide and rotate eyeball to thoroughly wash the eye
- rinse cup with clean water after each use
- replace cap after use

Other information

- store at 15-25ºC (59-77ºF)
- keep tightly closed
- does not contain thimerosal
- enclosed eye cup is sterile if packaging is intact
- use before expiration date marked on the carton or bottle

Inactive ingredients

boric acid, sodium borate and sodium chloride.

PRESERVATIVE ADDED: benzalkonium chloride (0.01%)

Questions or comments?

Call: 1-888-527-4276